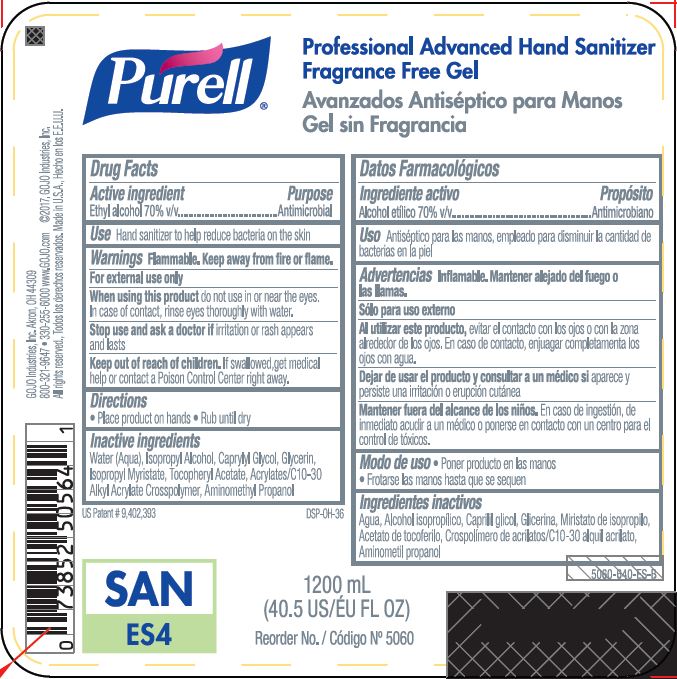 DRUG LABEL: PURELL Professional Advanced Hand Sanitizer Fragrance Free Gel
NDC: 21749-717 | Form: GEL
Manufacturer: GOJO Industries, Inc.
Category: otc | Type: HUMAN OTC DRUG LABEL
Date: 20251219

ACTIVE INGREDIENTS: ALCOHOL 0.7 mL/1 mL
INACTIVE INGREDIENTS: WATER; ISOPROPYL ALCOHOL; CAPRYLYL GLYCOL; GLYCERIN; ISOPROPYL MYRISTATE; .ALPHA.-TOCOPHEROL ACETATE, D-; CARBOMER INTERPOLYMER TYPE A (ALLYL SUCROSE CROSSLINKED); AMINOMETHYLPROPANOL

PURELL Professional Advanced Hand Sanitizer Fragrance Free Gel

Active ingredient

Ethyl alcohol 70% v/v

Purpose

Antimicrobial

Uses

- Hand sanitizer to help reduce bacteria on the skin that cause disease
- Recommended for repeated use

Warnings

Flammable. Keep away from fire or flame.

For external use only

WHEN USING

When using this productdo not use in or near the eyes. In case of contact, rinse eyes thoroughly with water.

Stop use and ask a doctor ifirritation or rash appears and lasts

Keep Out of Reach of Children. If swallowed, get medical help or contact a Poison Control Center right away.

Directions

- Place product on hands
- Run until dry

Inactive ingredients

Water (Aqua), Isopropyl Alcohol, PEG-12 Dimethicone, Caprylyl Glycol, Glycerin, Isopropyl Myristate, Tocopheryl Acetate, Acrylates/C10-30 Alkyl Acrylate Crosspolymer, Aminomethyl Propanol